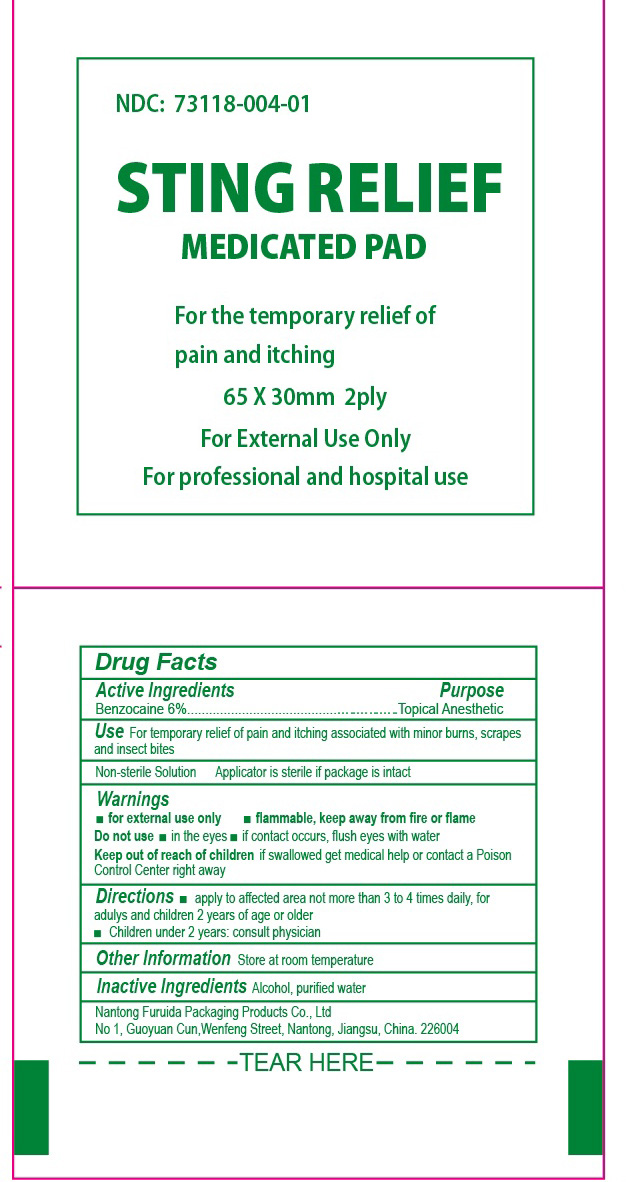 DRUG LABEL: STING RELIEF MEDICATED PAD
NDC: 73118-004 | Form: SWAB
Manufacturer: Nantong Furuida Packaging Products Co., Ltd.
Category: otc | Type: HUMAN OTC DRUG LABEL
Date: 20210524

ACTIVE INGREDIENTS: BENZOCAINE 0.06 mg/1 1
INACTIVE INGREDIENTS: ALCOHOL; WATER

73118-004sting relief

Active Ingredient

Medicinal Ingredient:Benzocaine6%

PURPOSE

Topical Anesthetic

Use

For the temporary relief of pain and itching associated with minor burns, scrapes and insect bites

Directions

Apply to affected area not more than 3 to 4 times daily. For adults and children 2 years of age and older. Children under 2 years: consult a physician.

Warnings

FOR EXTERNAL USE ONLY.FLAMMABLE,Keep away from fire or flame.

Do not use in the eyes ,if contact occurs ,flush eyes with water.

other information sotre at room temperature 15OC-30OC(59-86OF)

KEEP OUT OF REACH OF CHILDREN. if swallowed get medical help or contact a Poison Control Center right away.

Inactive Ingredients

isopropyl alcohol,purified water